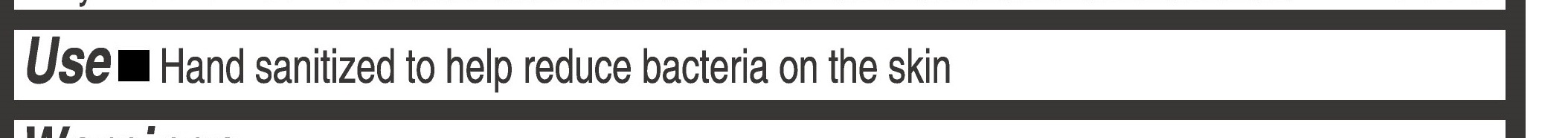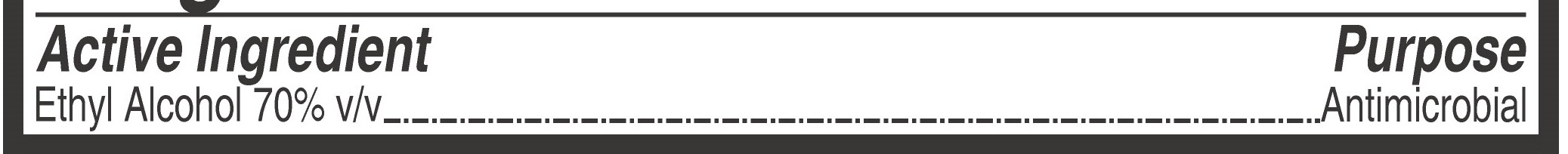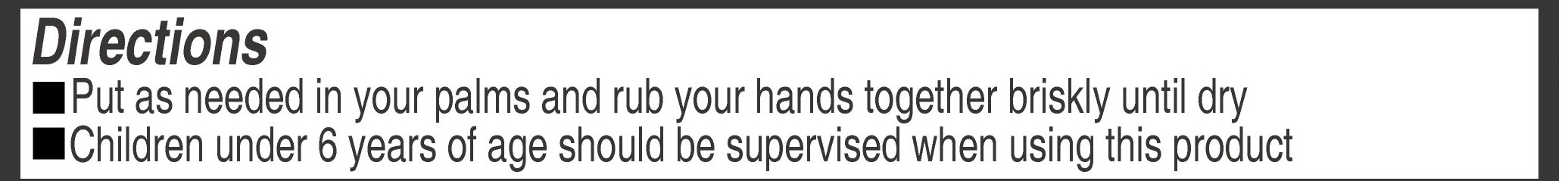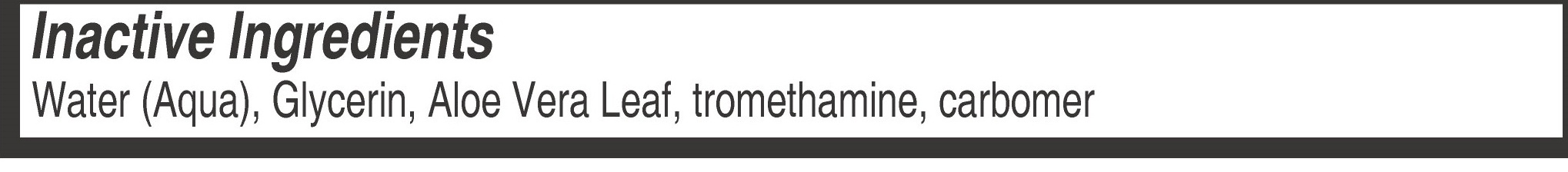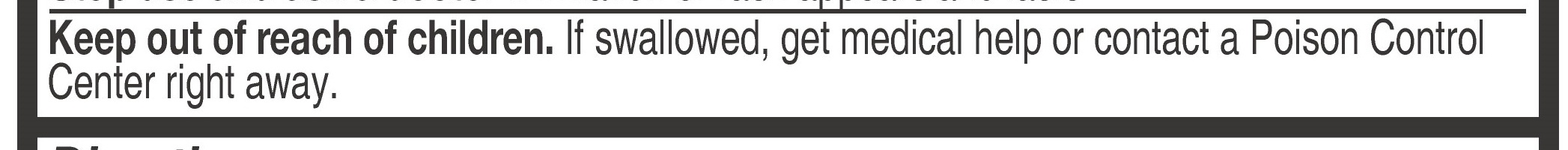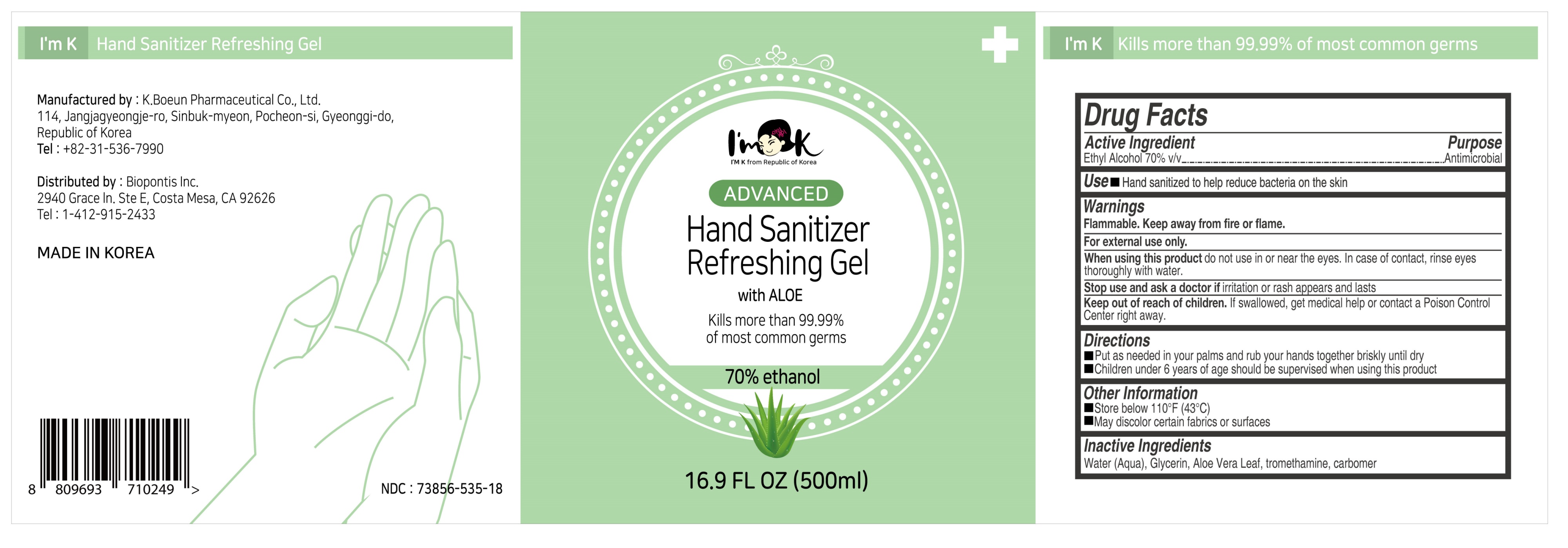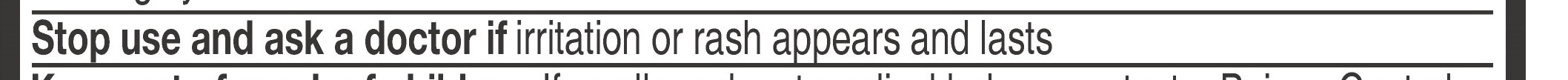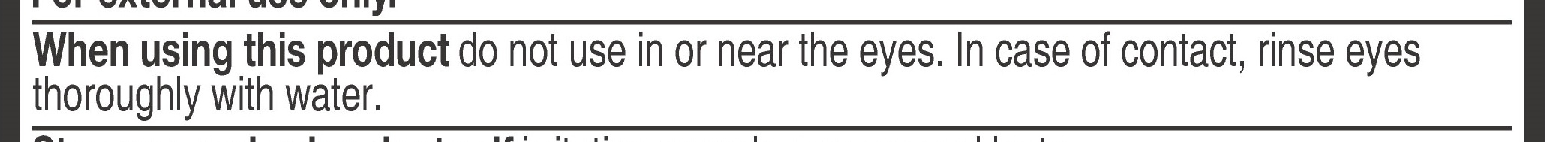 DRUG LABEL: ImK hand sanitizer
NDC: 73856-535 | Form: GEL
Manufacturer: Biopontis inc
Category: otc | Type: HUMAN OTC DRUG LABEL
Date: 20200617

ACTIVE INGREDIENTS: ALCOHOL 350 mL/500 mL
INACTIVE INGREDIENTS: GLYCERIN; CARBOMER 940; WATER; TROMETHAMINE; ALOE

This is a hand sanitizer manufactured according to the Temporary Policy for Preparation of Certain Alcohol-Based Hand Sanitizer Products During the Public Health Emergency (CoViD-19); Guidance for Industry.

The hand sanitizer is manufactured using only the following United States Pharmacopoeia (USP) grade ingredients in the preparation of the product (percentage in final product formulation) consistent with World Health Organization (WHO) recommendations:

1. Alcohol (ethanol) (USP or Food Chemical Codex (FCC) grade) (80%, volume/volume (v/v)) in an aqueous solution denatured according to Alcohol and Tobacco Tax and Trade Bureau regulations in 27 CFR part 20.
2. Glycerol (1.45% v/v).
3. Hydrogen peroxide (0.125% v/v).
4. Sterile distilled water or boiled cold water.

The firm does not add other active or inactive ingredients. Different or additional ingredients may impact the quality and potency of the product.

Active Ingredient(s)

Alcohol 70% v/v. Purpose: Antiseptic

Purpose

Antiseptic, Hand Sanitizer

Use

Hand sanitized to help reduce bacteria on the skin

Warnings

For external use only. Flammable. Keep away from heat or flame

Do not use

Stop use and ask a doctor if irritation or rash appears and lasts

WHEN USING

When using the product do not use in or near the eyes. in case of contact, rinse eyes thoroughly with water.

Stop use and ask a doctor if irritation or rash appears and lasts

Keep out of reach of children. If swallowed, get medical help or contact a Poison Control Center right away.

Directions

- Put as needed in your palms and rub your hands together briskly until dry
- Children under 6 years of age should be supervised when using this product

Other information

- Store between 15-30C (59-86F)
- Avoid freezing and excessive heat above 40C (104F)

Inactive ingredients

Water(aqua), Glycerin, Aloe Vera Leaf, Tromethamine, Carbomer

Package Label - Principal Display Panel

500 ml NDC:73856-535-18